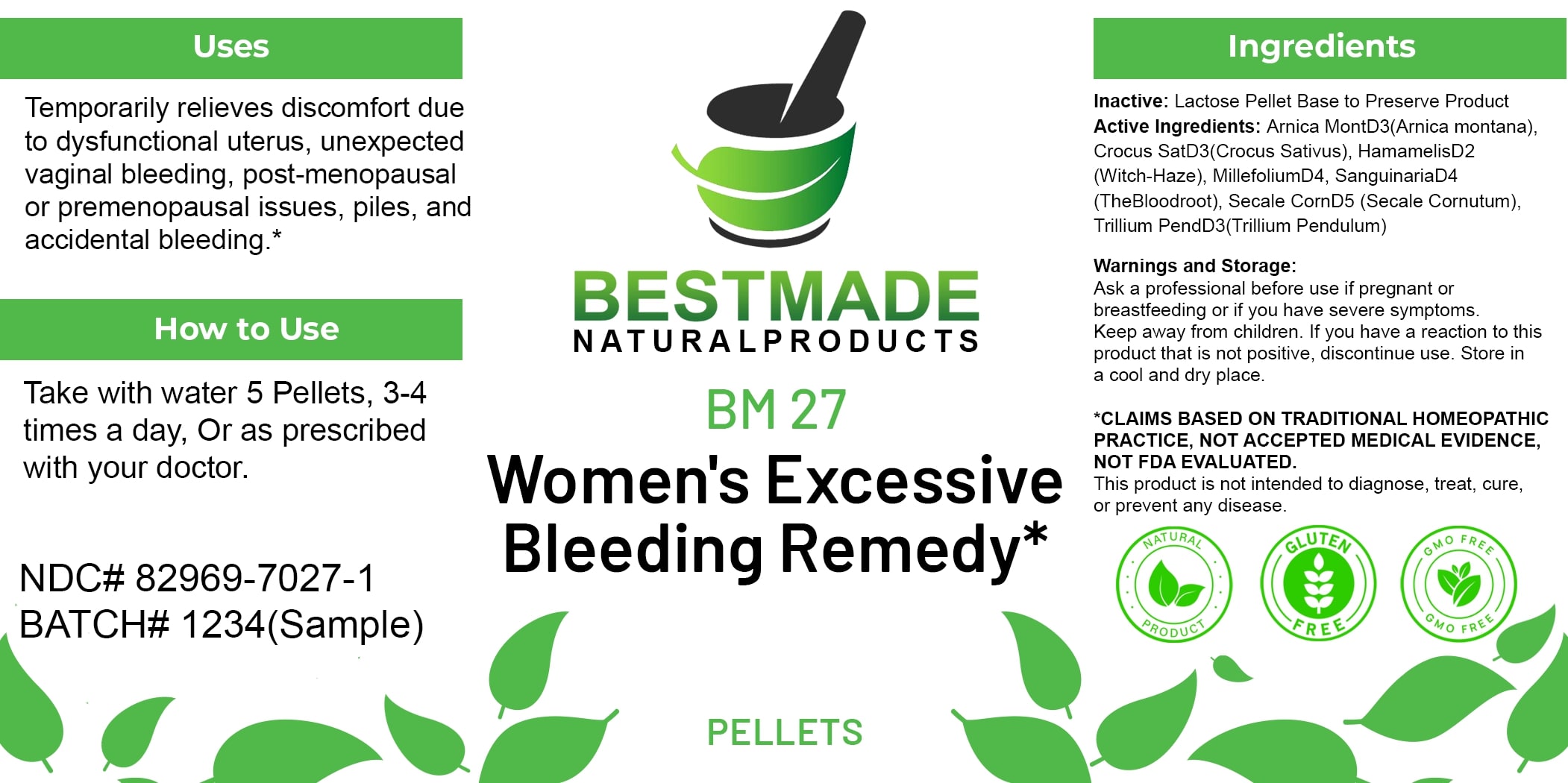 DRUG LABEL: Bestmade Natural Products BM27 Pellets
NDC: 82969-7027 | Form: TABLET, SOLUBLE
Manufacturer: Bestmade Natural Products
Category: homeopathic | Type: HUMAN OTC DRUG LABEL
Date: 20250408

ACTIVE INGREDIENTS: CLAVICEPS PURPUREA SCLEROTIUM 30 [hp_C]/30 [hp_C]; HAMAMELIS VIRGINIANA ROOT BARK/STEM BARK 30 [hp_C]/30 [hp_C]; SAFFRON 30 [hp_C]/30 [hp_C]; ARNICA MONTANA WHOLE 30 [hp_C]/30 [hp_C]; TRILLIUM ERECTUM ROOT 30 [hp_C]/30 [hp_C]; ACHILLEA MILLEFOLIUM WHOLE 30 [hp_C]/30 [hp_C]; SANGUINARIA CANADENSIS ROOT 30 [hp_C]/30 [hp_C]
INACTIVE INGREDIENTS: LACTOSE 30 [hp_C]/30 [hp_C]

BM27 Pellets

DOSAGE AND ADMINISTRATION

How to Use

Take with water 5 Pellets, 3-4 times a day, Or as prescribed with your doctor.

INACTIVE INGREDIENT

Ingredients

Inactive: Lactose Pellet Base to Preserve Product

ACTIVE INGREDIENT

Active Ingredients: Arnica MontD3(Arnica montana), Crocus SatD3(Crocus Sativus), HamamelisD2 (Witch-Hazel), MillefoliumD4, SanguinariaD4 (TheBloodroot), Secale CornD5 (Secale Cornutum), Trillium PendD3(Trillium Pendulum)

Uses

Temporarily relieves discomfort due to dysfunctional uterus, unexpected vaginal bleeding, post-menopausal or premenopausal issues, piles, and accidental bleeding.*

*CLAIMS BASED ON TRADITIONAL HOMEOPATHIC PRACTICE. NOT ACCEPTED MEDICAL EVIDENCE. NOT FDA EVALUATED.

This product is not intended to diagnose, treat, cure, or prevent any disease.

Uses

Temporarily relieves discomfort due to dysfunctional uterus, unexpected vaginal bleeding, post-menopausal or premenopausal issues, piles, and accidental bleeding.*

*CLAIMS BASED ON TRADITIONAL HOMEOPATHIC PRACTICE. NOT ACCEPTED MEDICAL EVIDENCE. NOT FDA EVALUATED.

This product is not intended to diagnose, treat, cure, or prevent any disease.

KEEP OUT OF REACH OF CHILDREN

Warnings and Storage:

Ask a professional before use if pregnant or breastfeeding or if you have severe symptoms. Keep away from children. If you have a reaction to this product that is not positive, discontinue use. Store in a cool and dry place.

Warnings and Storage:

Ask a professional before use if pregnant or breastfeeding or if you have severe symptoms. Keep away from children. If you have a reaction to this product that is not positive, discontinue use. Store in a cool and dry place.

*CLAIMS BASED ON TRADITIONAL HOMEOPATHIC PRACTICE. NOT ACCEPTED MEDICAL EVIDENCE. NOT FDA EVALUATED.

This product is not intended to diagnose, treat, cure, or prevent any disease.

Entire package label